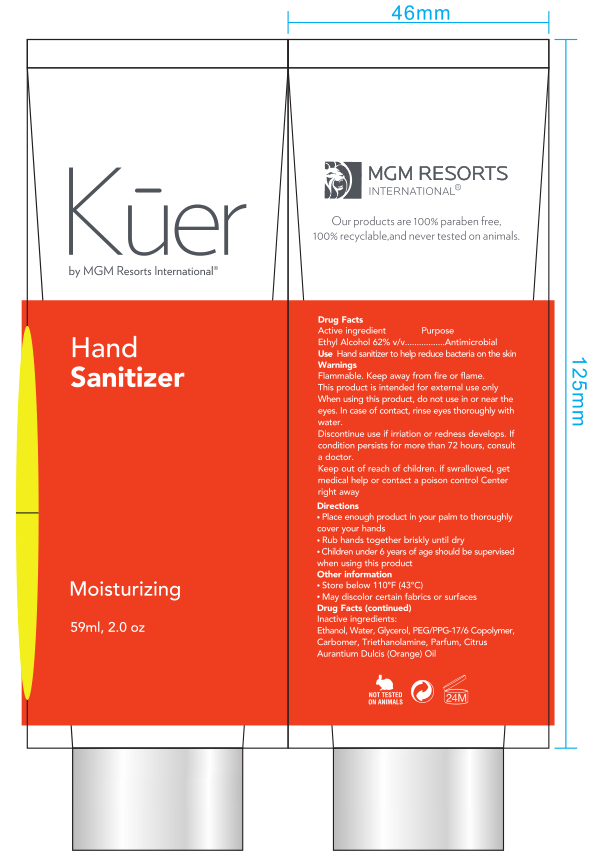 DRUG LABEL: HAND SANITIZER
NDC: 52692-001 | Form: GEL
Manufacturer: Guangdong Songtaixing Cosmetics Industry Co., Ltd
Category: otc | Type: HUMAN OTC DRUG LABEL
Date: 20200713

ACTIVE INGREDIENTS: ALCOHOL 36.58 mL/59 mL
INACTIVE INGREDIENTS: PEG/PPG-17/6 COPOLYMER; FRAGRANCE LAVENDER & CHIA F-153480; WATER; TROLAMINE; ORANGE OIL; GLYCERIN; CARBOMER HOMOPOLYMER, UNSPECIFIED TYPE

DOSAGE AND ADMINISTRATION

Store below 110°F (43°C)

INACTIVE INGREDIENT

Water,Glycerol, PEG/PPG-17/6 Copolymer,Carbomer,Triethanolamine,Parfum,Citrus Aurantium Dulcis(Orange) Oil

INDICATIONS AND USAGE

Place enough product in your palm to thoroughly cover your hands.Rub hands together briskly until dry

ACTIVE INGREDIENT

Ethanol

keep out of reach of children

PURPOSE

Disinfection
Sterilization
No Rinseing

WARNINGS

Flammable, keep away from fire or flame .